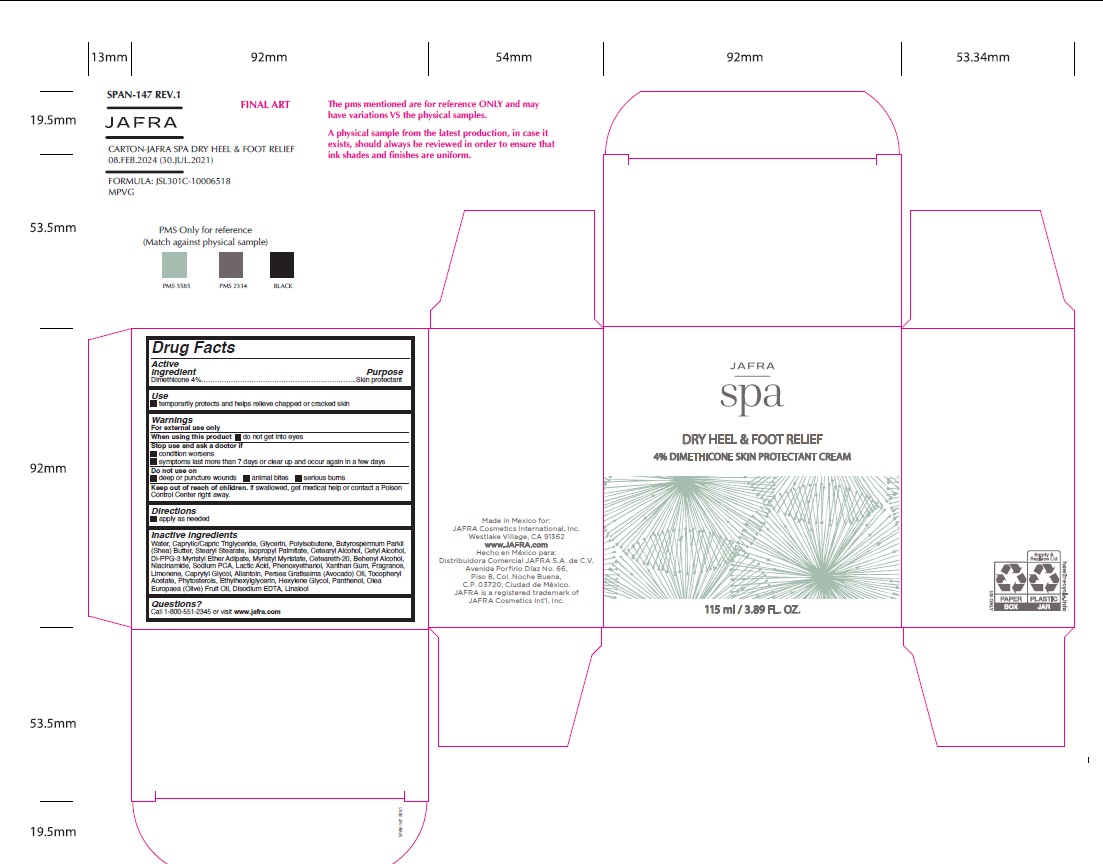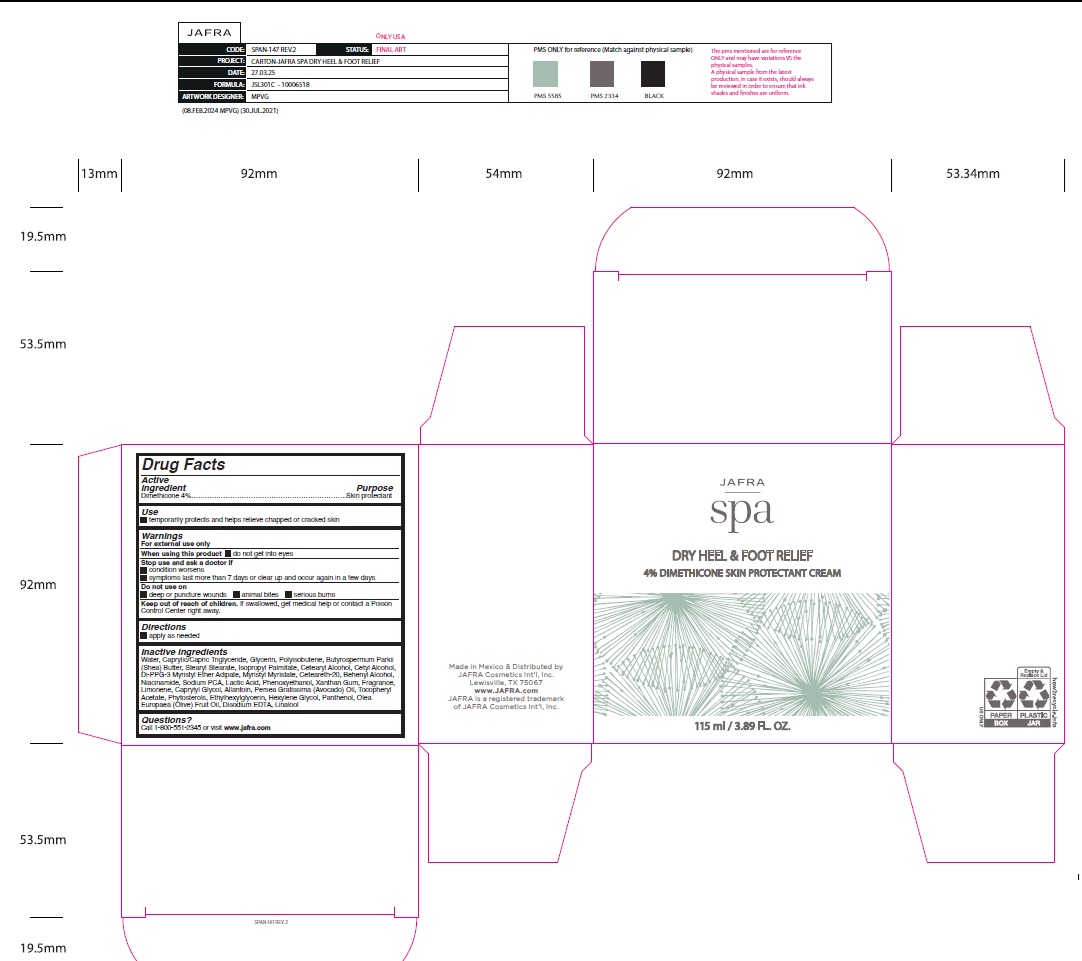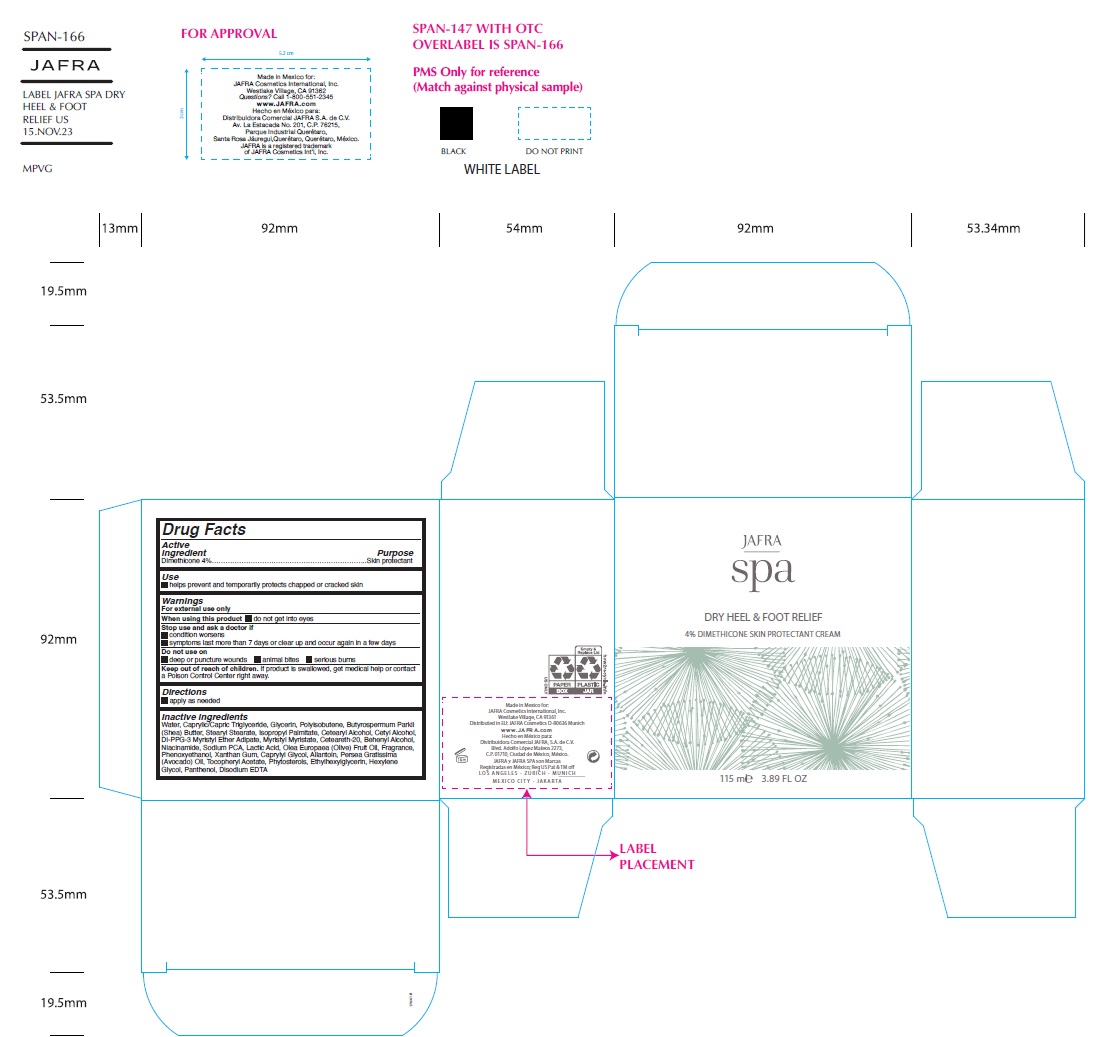 DRUG LABEL: Spa Dry Heel Foot Relief
NDC: 68828-002 | Form: CREAM
Manufacturer: Distribuidora Comercial Jafra, S.A. de C.V.
Category: otc | Type: HUMAN OTC DRUG LABEL
Date: 20251105

ACTIVE INGREDIENTS: DIMETHICONE 4 g/100 mL
INACTIVE INGREDIENTS: WATER; MEDIUM-CHAIN TRIGLYCERIDES; GLYCERIN; POLYISOBUTYLENE (55000 MW); SHEA BUTTER; STEARYL STEARATE; ISOPROPYL PALMITATE; CETOSTEARYL ALCOHOL; CETYL ALCOHOL; DI-PPG-3 MYRISTYL ETHER ADIPATE; MYRISTYL MYRISTATE; POLYOXYL 20 CETOSTEARYL ETHER; DOCOSANOL; NIACINAMIDE; SODIUM PYRROLIDONE CARBOXYLATE; LACTIC ACID, UNSPECIFIED FORM; OLIVE OIL; PHENOXYETHANOL; XANTHAN GUM; CAPRYLYL GLYCOL; ALLANTOIN; AVOCADO OIL; .ALPHA.-TOCOPHEROL ACETATE; ETHYLHEXYLGLYCERIN; HEXYLENE GLYCOL; PANTHENOL; EDETATE DISODIUM; LIMONENE, (+)-; LINALOOL, (+/-)-

Active ingredient

Dimethicone 4%

Purpose

Skin protectant

Uses

- temporarily protects and helps relieve chapped or cracked skin

Warnings

For external use only
When using this product● do not get into eyes
Stop use and ask a doctor● condition worsens ● symptoms last more than 7 days or clear up and occur again in a few days
Do not use on● deep or puncture wounds ● animal bites ● serious burns
Keep out of reach of children. If swallowed, get medical help or contact a Poison Control Center right away.

Directions

• apply as needed

Inactive ingredients

Water, Caprylic/Capric Triglyceride, Glycerin, Polyisobutene, Butyrospermum Parkii (Shea) Butter, Stearyl Stearate, Isopropyl Palmitate, Cetearyl Alcohol, Cetyl Alcohol, Di-PPG-3 Myristyl Ether Adipate, Myristyl Myristate, Ceteareth-20, Behenyl Alcohol, Niacinamide, Sodium PCA, Lactic Acid, Phenoxyethanol , Xanthan Gum, Fragrance, Limonene, Caprylyl Glycol, Allantoin, Persea Gratissima (Avocado) Oil, Tocopheryl Acetate, Phytosterols, Ethylhexylglycerin, Hexylene Glycol, Panthenol, Olea Europaea (Olive) Fruit Oil, Disodium EDTA, Linalool

Questions?Call 1-800-551-2345 or visit www.jafra.com